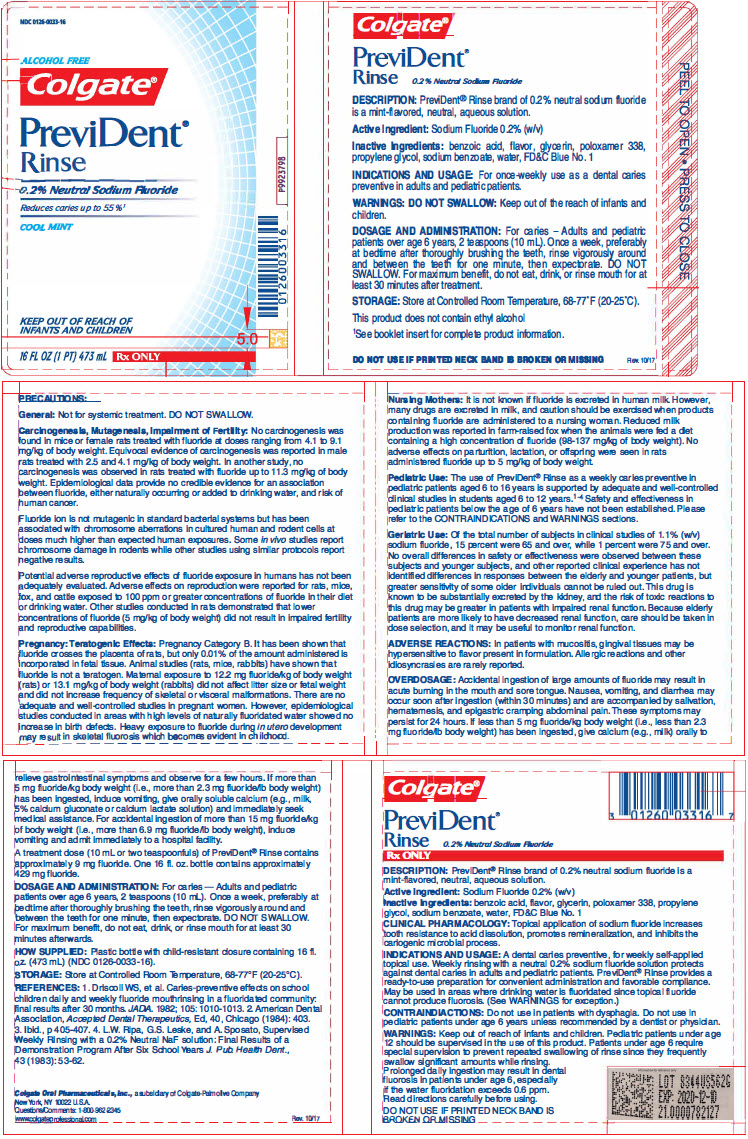 DRUG LABEL: PreviDent Alcohol Free
NDC: 0126-0033 | Form: MOUTHWASH
Manufacturer: Colgate Oral Pharmaceuticals, Inc.
Category: prescription | Type: HUMAN PRESCRIPTION DRUG LABEL
Date: 20220711

ACTIVE INGREDIENTS: SODIUM FLUORIDE 0.9 mg/1 mL
INACTIVE INGREDIENTS: BENZOIC ACID; GLYCERIN; POLOXAMER 338; PROPYLENE GLYCOL; SODIUM BENZOATE; WATER; FD&C BLUE NO. 1

Colgate® PreviDent® Rinse

0.2% Neutral Sodium Fluoride

Rx ONLY

DESCRIPTION

PreviDent® Rinse brand of 0.2% neutral sodium fluoride is a mint-flavored, neutral, aqueous solution.

Active Ingredient

Sodium Fluoride 0.2% (w/v)

Inactive Ingredients

Benzoic Acid, Flavor, Glycerin, Poloxamer 338, Propylene Glycol, Sodium Benzoate, Water, FD&C Blue No. 1

CLINICAL PHARMACOLOGY

Topical application of sodium fluoride increases tooth resistance to acid dissolution, promotes remineralization, and inhibits the cariogenic microbial process.

INDICATIONS AND USAGE

A dental caries preventive, for weekly self-applied topical use. Weekly rinsing with a neutral 0.2% sodium fluoride solution protects against dental caries in adults and pediatric patients. PreviDent® Rinse provides a ready-to-use preparation for convenient administration and favorable compliance. May be used in areas where drinking water is fluoridated since topical fluoride cannot produce fluorosis. (See WARNINGS for exception.)

CONTRAINDIACTIONS

Do not use in patients with dysphagia. Do not use in pediatric patients under age 6 years unless recommended by a dentist or physician.

WARNINGS

Keep out of reach of infants and children. Pediatric patients under age 12 should be supervised in the use of this product. Patients under age 6 require special supervision to prevent repeated swallowing of rinse since they frequently swallow significant amounts while rinsing. Prolonged daily ingestion may result in dental fluorosis in patients under age 6, especially if the water fluoridation exceeds 0.6 ppm. Read directions carefully before using.

DO NOT USE IF PRINTED NECK BAND IS BROKEN OR MISSING

PRECAUTIONS

General

Not for systemic treatment. DO NOT SWALLOW.

Carcinogenesis, Mutagenesis, Impairment of Fertility

No carcinogenesis was found in mice or female rats treated with fluoride at doses ranging from 4.1 to 9.1 mg/kg of body weight. Equivocal evidence of carcinogenesis was reported in male rats treated with 2.5 and 4.1 mg/kg of body weight. In another study, no carcinogenesis was observed in rats treated with fluoride up to 11.3 mg/kg of body weight. Epidemiological data provide no credible evidence for an association between fluoride, either naturally occurring or added to drinking water, and risk of human cancer.

Fluoride ion is not mutagenic in standard bacterial systems but has been associated with chromosome aberrations in cultured human and rodent cells at doses much higher than expected human exposures. Some in vivo report chromosome damage in rodents while other studies using similar protocols report negative results.

Potential adverse reproductive effects of fluoride exposure in humans has not been adequately evaluated. Adverse effects on reproduction were reported for rats, mice, fox, and cattle exposed to 100 ppm or greater concentrations of fluoride in their diet or drinking water. Other studies conducted in rats demonstrated that lower concentrations of fluoride (5 mg/kg of body weight) did not result in impaired fertility and reproductive capabilities.

Pregnancy

Teratogenic Effects

Pregnancy Category B

It has been shown that fluoride crosses the placenta of rats, but only 0.01% of the amount administered is incorporated in fetal tissue. Animal studies (rats, mice, rabbits) have shown that fluoride is not a teratogen. Maternal exposure to 12.2 mg fluoride/kg of body weight (rats) or 13.1 mg/kg of body weight (rabbits) did not affect litter size or fetal weight and did not increase frequency of skeletal or visceral malformations. There are no adequate and well-controlled studies in pregnant women. However, epidemiological studies conducted in areas with high levels of naturally fluoridated water showed no increase in birth defects. Heavy exposure to fluoride during in utero development may result in skeletal fluorosis which becomes evident in childhood.

Nursing Mothers

It is not known if fluoride is excreted in human milk. However, many drugs are excreted in milk, and caution should be exercised when products containing fluoride are administered to a nursing woman. Reduced milk production was reported in farm-raised fox when the animals were fed a diet containing a high concentration of fluoride (98-137 mg/kg of body weight). No adverse effects on parturition, lactation, or offspring were seen in rats administered fluoride up to 5 mg/kg of body weight.

Pediatric Use

The use of PreviDent® Rinse as a weekly caries preventive in pediatric patients aged 6 to 16 years is supported by adequate and well-controlled clinical studies in students aged 6 to 12 years.^1-4 Safety and effectiveness in pediatric patients below the age of 6 years have not been established. Please refer to the CONTRAINDICATIONS and WARNINGS sections.

Geriatric Use

Of the total number of subjects in clinical studies of 1.1% (w/v) sodium fluoride, 15 percent were 65 and over, while 1 percent were 75 and over. No overall differences in safety or effectiveness were observed between these subjects and younger subjects, and other reported clinical experience has not identified differences in responses between the elderly and younger patients, but greater sensitivity of some older individuals cannot be ruled out. This drug is known to be substantially excreted by the kidney, and the risk of toxic reactions to this drug may be greater in patients with impaired renal function. Because elderly patients are more likely to have decreased renal function, care should be taken in dose selection, and it may be useful to monitor renal function.

ADVERSE REACTIONS

In patients with mucositis, gingival tissues may be hypersensitive to flavor present in formulation. Allergic reactions and other idiosyncrasies are rarely reported.

OVERDOSAGE

Accidental ingestion of large amounts of fluoride may result in acute burning in the mouth and sore tongue. Nausea, vomiting, and diarrhea may occur soon after ingestion (within 30 minutes) and are accompanied by salivation, hematemesis, and epigastric cramping abdominal pain. These symptoms may persist for 24 hours. If less than 5 mg fluoride/kg body weight (i.e., less than 2.3 mg fluoride/lb body weight) has been ingested, give calcium (e.g., milk) orally to relieve gastrointestinal symptoms and observe for a few hours. If more than 5 mg fluoride/kg body weight (i.e., more than 2.3 mg fluoride/lb body weight) has been ingested, induce vomiting, give orally soluble calcium (e.g., milk, 5% calcium gluconate or calcium lactate solution) and immediately seek medical assistance. For accidental ingestion of more than 15 mg fluoride/kg of body weight (i.e., more than 6.9 mg fluoride/lb body weight), induce vomiting and admit immediately to a hospital facility.

A treatment dose (10 mL or two teaspoonfuls) of PreviDent® Rinse contains approximately 9 mg fluoride. One 16 fl. oz. bottle contains approximately 429 mg fluoride.

DOSAGE AND ADMINISTRATION

For caries — Adults and pediatric patients over age 6 years, 2 teaspoons (10 mL). Once a week, preferably at bedtime after thoroughly brushing the teeth, rinse vigorously around and between the teeth for one minute, then expectorate. DO NOT SWALLOW. For maximum benefit, do not eat, drink, or rinse mouth for at least 30 minutes afterwards.

HOW SUPPLIED

Plastic bottle with child-resistant closure containing 16 fl. oz. (473 mL) (NDC 0126-0033-16).

STORAGE

Store at Controlled Room Temperature, 68-77°F (20-25°C).

REFERENCES

1. Driscoll WS, et al. Caries-preventive effects on school children daily and weekly fluoride mouthrinsing in a fluoridated community: final results after 30 months. JADA. 1982; 105: 1010-1013. 2. American Dental Association, Accepted Dental Therapeutics, Ed, 40, Chicago (1984): 403. 3. Ibid., p 405-407. 4. L.W. Ripa, G.S. Leske, and A. Sposato, Supervised Weekly Rinsing with a 0.2% Neutral NaF solution: Final Results of a Demonstration Program After Six School Years J. Pub. Health Dent.,43 (1983): 53-62.

Colgate Oral Pharmaceuticals, Inc., a subsidiary of Colgate-Palmolive Company
New York, NY 10022 U.S.A.
Questions/Comments: 1-800-962-2345
www.colgateprofessional.com

P9913793
Rev. Jan 2016

PRINCIPAL DISPLAY PANEL - 473 mL Bottle Label

NDC 0126-0033-16

ALCOHOL FREE
Colgate®

PreviDent®
Rinse

0.2% Neutral Sodium Fluoride
Reduces caries up to 55%^1
COOL MINT

KEEP OUT OF REACH OF
INFANTS AND CHILDREN

16 FL OZ (1 PT) 473 mL
Rx ONLY

P9923798